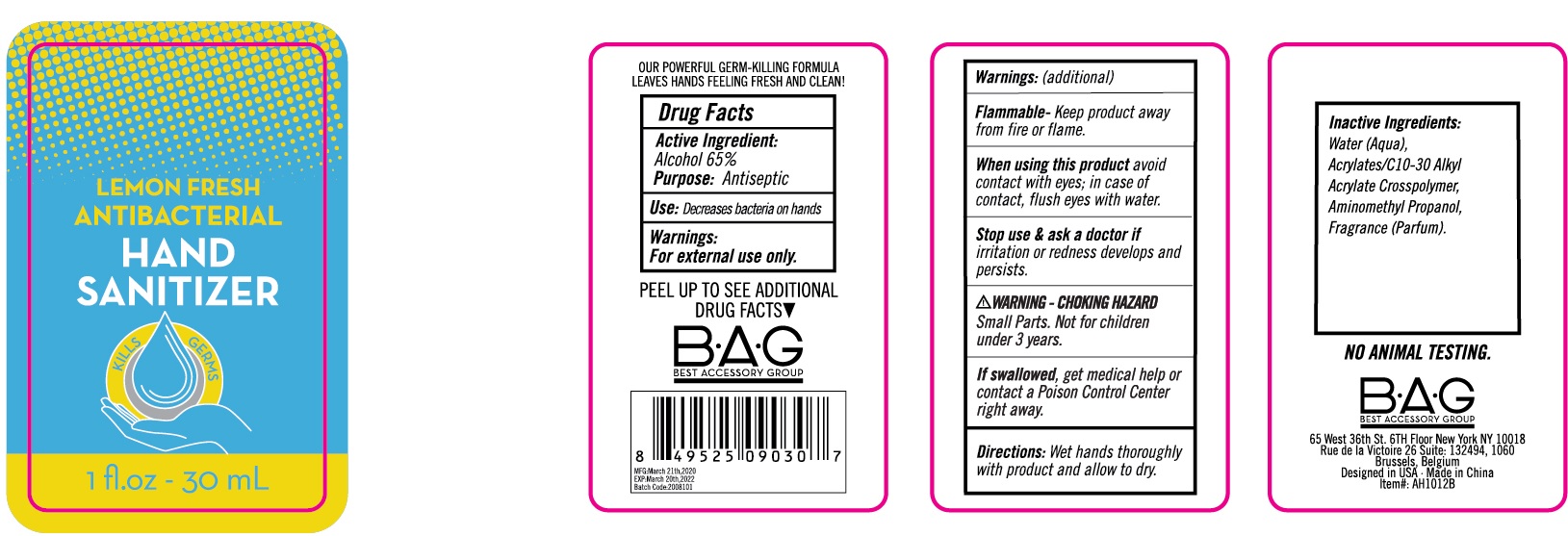 DRUG LABEL: Lemon Fresh Antibacterial Hand Sanitizer
NDC: 56136-028 | Form: SOLUTION
Manufacturer: Ganzhou Olivee Cosmetic Co., Ltd.
Category: otc | Type: HUMAN OTC DRUG LABEL
Date: 20200323

ACTIVE INGREDIENTS: ALCOHOL 65 mL/100 mL
INACTIVE INGREDIENTS: WATER; AMINOMETHYLPROPANOL

Active ingredient

Alcohol 65%

Purpose

Antiseptic

Use

Decreases bacteria on hands.

Warnings

For external use only.

Flammable,

Keep product away from fire or flame.

When using this product

avoid contact with eyes; in case of contact, flush eyes with water.

Stop use and ask a doctor if

irritation or redness develops and persists.

Keep out of reach of children.

If swallowed, get medical help or contact a Poison Control Center right away.

Directions

Wet hands thoroughly with product and allow to dry.

Inactive ingredients

Water (Aqua), Acrylates/C10-30 Alkyl Acrylate Crosspolymer, Aminomethyl Propanol, Fragrance (Parfum)

Best Accessory Group

65 West 36th St. 6th Floor New York NY 10018

Rue de la Victoire 26 Suite: 132494, 1060

Brussels, Belgium

Designed in USA . Made in China

Item#: AH1012B